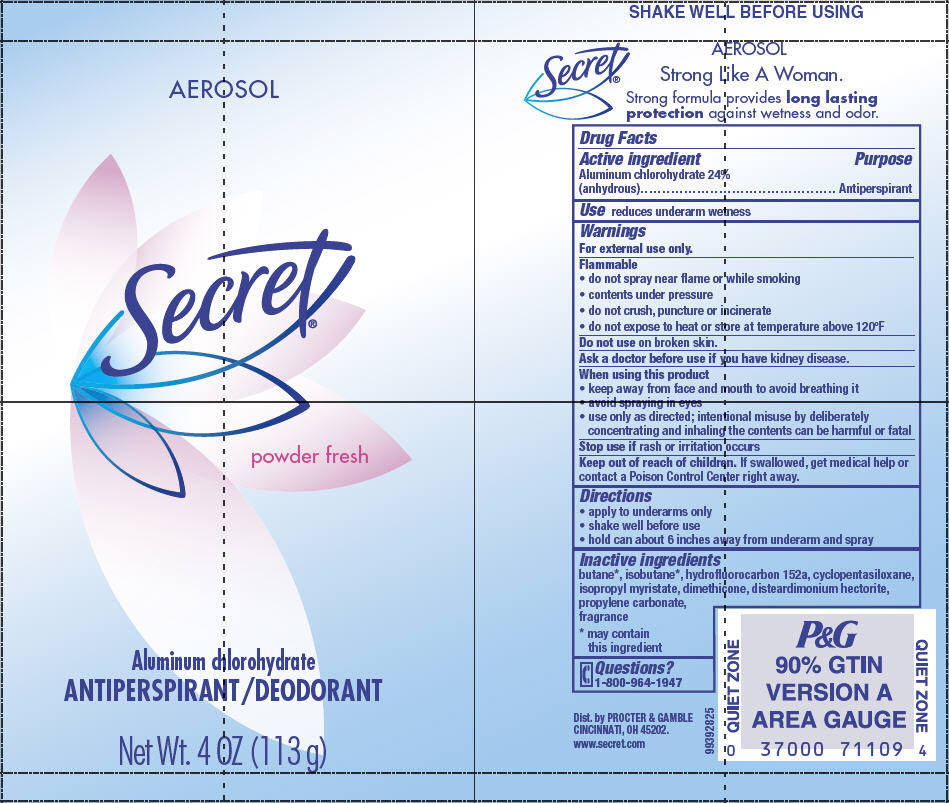 DRUG LABEL: Secret Antiperspirant
NDC: 37000-134 | Form: AEROSOL, SPRAY
Manufacturer: The Procter & Gamble Manufacturing Company
Category: otc | Type: HUMAN OTC DRUG LABEL
Date: 20251201

ACTIVE INGREDIENTS: ALUMINUM CHLOROHYDRATE 0.24 g/1 g
INACTIVE INGREDIENTS: BUTANE; ISOBUTANE; 1,1-DIFLUOROETHANE; CYCLOMETHICONE 5; ISOPROPYL MYRISTATE; DIMETHICONE; PROPYLENE CARBONATE

Secret®
powder fresh

Drug Facts

Active ingredient

Aluminum chlorohydrate 24% (anhydrous)

Purpose

Antiperspirant

Use

reduces underarm wetness

Warnings

For external use only.

Flammable

- do not spray near flame or while smoking
- contents under pressure
- do not crush, puncture or incinerate
- do not expose to heat or store at temperature above 120°F

Do not use on broken skin.

Ask a doctor before use if you have kidney disease.

When using this product

- keep away from face and mouth to avoid breathing it
- avoid spraying in eyes
- use only as directed; intentional misuse by deliberately concentrating and inhaling the contents can be harmful or fatal

Stop use if rash or irritation occurs

Keep out of reach of children. If swallowed, get medical help or contact a Poison Control Center right away.

Directions

- apply to underarms only
- shake well before use
- hold can about 6 inches away from underarm and spray

Inactive ingredients

butane [may contain this ingredient] , isobutane , hydrofluorocarbon 152a, cyclopentasiloxane, isopropyl myristate, dimethicone, disteardimonium hectorite, propylene carbonate, fragrance

Questions?

1-800-964-1947

Dist. by PROCTER & GAMBLE
CINCINNATI, OH 45202.

PRINCIPAL DISPLAY PANEL - 113 g Can Label

AEROSOL

Secret®
powder fresh

Aluminum chlorohydrate
ANTIPERSPIRANT/DEODORANT

Net Wt. 4 OZ (113 g)